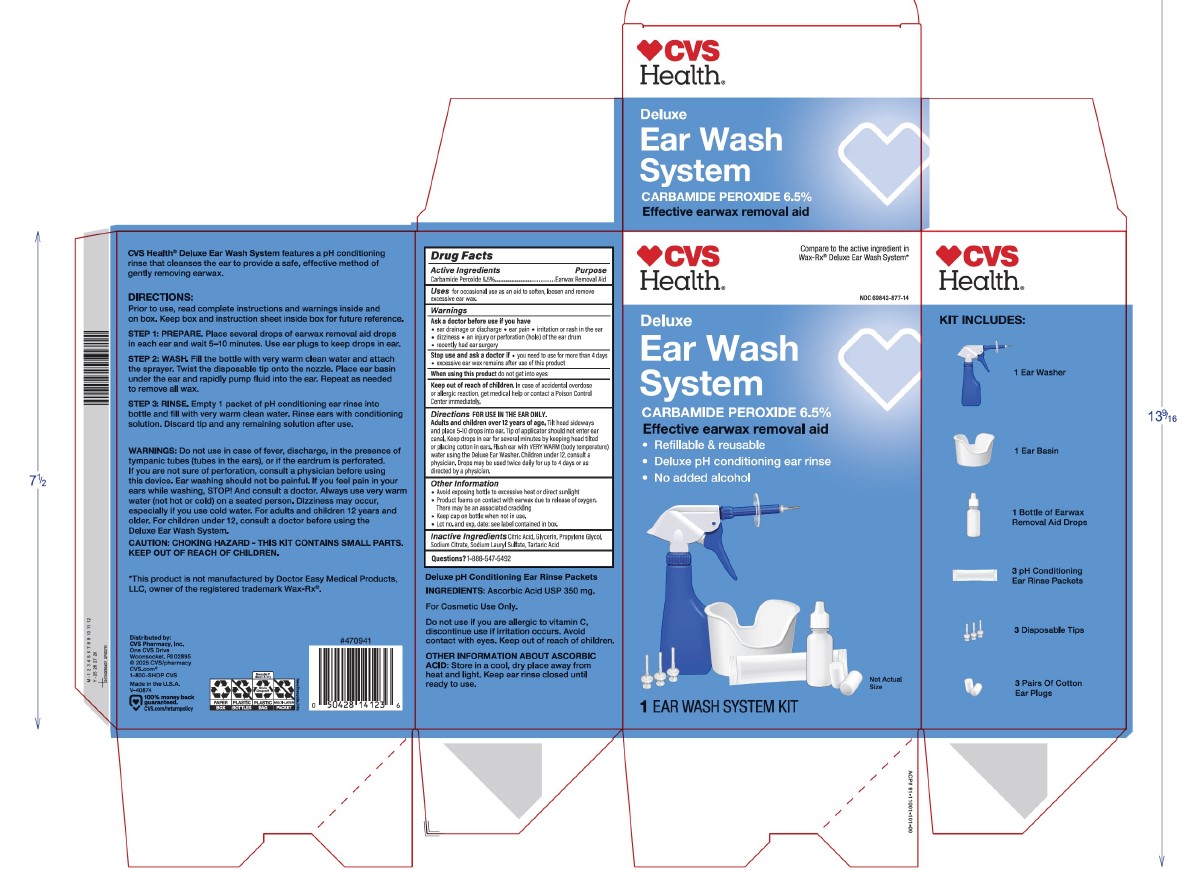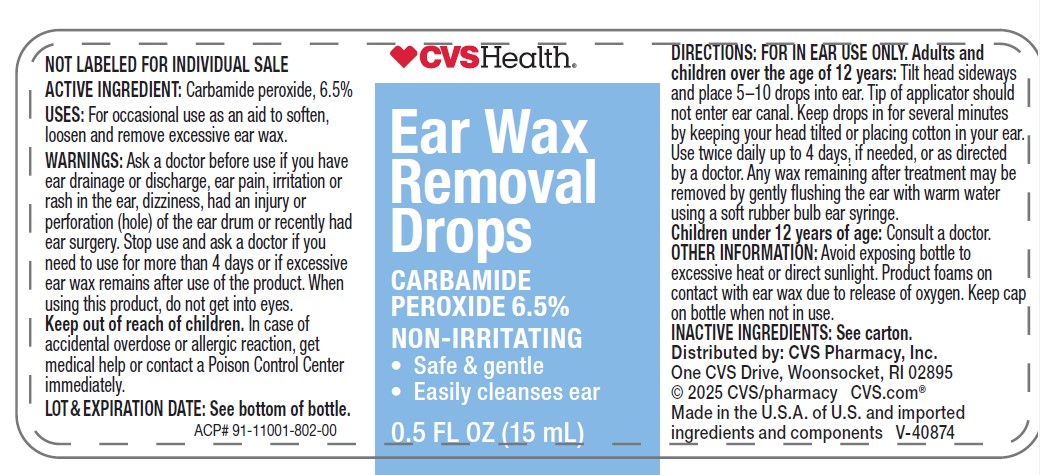 DRUG LABEL: Ear Wash Refill
NDC: 69842-877 | Form: KIT | Route: AURICULAR (OTIC)
Manufacturer: CVS
Category: otc | Type: HUMAN OTC DRUG LABEL
Date: 20260227

ACTIVE INGREDIENTS: CARBAMIDE PEROXIDE 65 mg/1 mL
INACTIVE INGREDIENTS: CITRIC ACID; GLYCERIN; PROPYLENE GLYCOL; SODIUM CITRATE; SODIUM LAURYL SULFATE; TARTARIC ACID

CVS Ear Wash Refill Kit

Drug Facts

Ear Wash Refill Kit Drug Facts

Active ingredient

Carbamide peroxide 6.5%____________Earwax removal aid

Purpose

Earwax removal aid

Uses

for occasional use as an aid to soften, loosen, and remove excessive earwax

Warnings

For use in the ear only

Ask a doctor before use if you have

- ear drainage or discharge
- ear pain
- irritation, or rash in the ear
- dizziness
- an injury or perforation (hole) of the ear drum
- recently had ear surgery

When using this product

- avoid contact with the eyes

Stop use and ask a doctor if

- you need to use for more than 4 days
- excessive earwax remains after use of this product

Keep out of reach of children.

If swallowed, get medical help or contact a Poison Control Center right away.

Directions

FOR USE IN THE EAR ONLY

Adults and children over 12 years of age:

- Tilt head sideways and place 5 to 10 drops into ear
- Tip of applicator should not enter ear canal
- Keep drops in ear for several minutes by keeping head tilted or placing cotton in the ear
- Flush ear with very warm (body temperature) water using the Deluxe Ear Washer
- Use twice daily for up to 4 days if needed, or as directed by a doctor
- Children Under 12 years:consult a doctor

Other information

- Avoid exposing bottle to excessive heat and direct sunlight
- Store bottle in the outer carton
- Keep cap in bottle when not in use
- Product foams on contact with earwax due to release of oxygen. There may be an assoiciated crackling sound.
- Do not use if tamper-evident safety seal is broken or missing

Inactive ingredients

citric acid, glycerin, propylene glycol, sodium citrate, sodium lauryl sulfate, water, tartaric acid

Questions?

1-888-547-5492